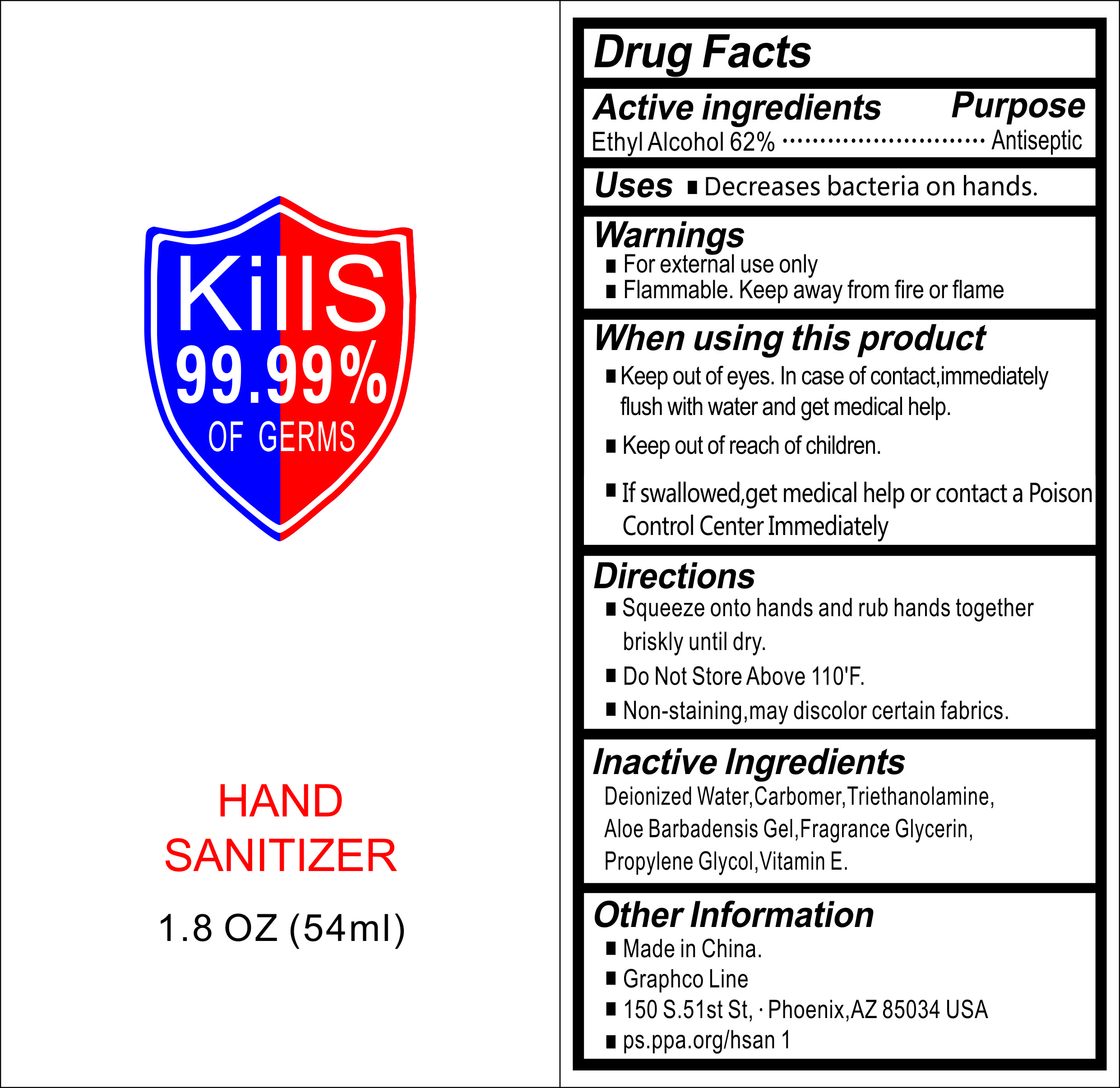 DRUG LABEL: Hand Sanitizer
NDC: 74746-002 | Form: GEL
Manufacturer: YUYAO WANGCHENG DAILY COMMODITY CO., LTD.
Category: otc | Type: HUMAN OTC DRUG LABEL
Date: 20221014

ACTIVE INGREDIENTS: ALCOHOL 62 mL/100 mL
INACTIVE INGREDIENTS: CARBOMER 934; WATER; PROPYLENE GLYCOL; TROLAMINE; ALOE VERA LEAF; ALPHA-TOCOPHEROL

74746-002 hand sanitizer 62% Alcohol

Active Ingredient(s)

Isopropyl Alcohol 62% v/v.

Purpose

Antiseptic

Use

Decreases bacteria on hands.

Warnings

■For external use only
1 Flammable. Keep away from fire or flame
When using this product
■Keep out of eyes. In case of contact, immediately
flush with water and get medical help.
■Keep out of reach of children.
■If swallowed, get medical help or contact a Poison
Control Center Immediately

Keep out of reach of children.

Directions

1 Squeeze onto hands and rub hands together
briskly until dry.
1 Do Not Store Above 110'F.
1 Non-staining, may discolor certain fabrics.

Inactive ingredients

Deionized Water, Carbomer,' Triethanolamine,
Aloe Barbadensis Gel, Fragrance Glycerin,
Propylene Glycol, Vitamin E.